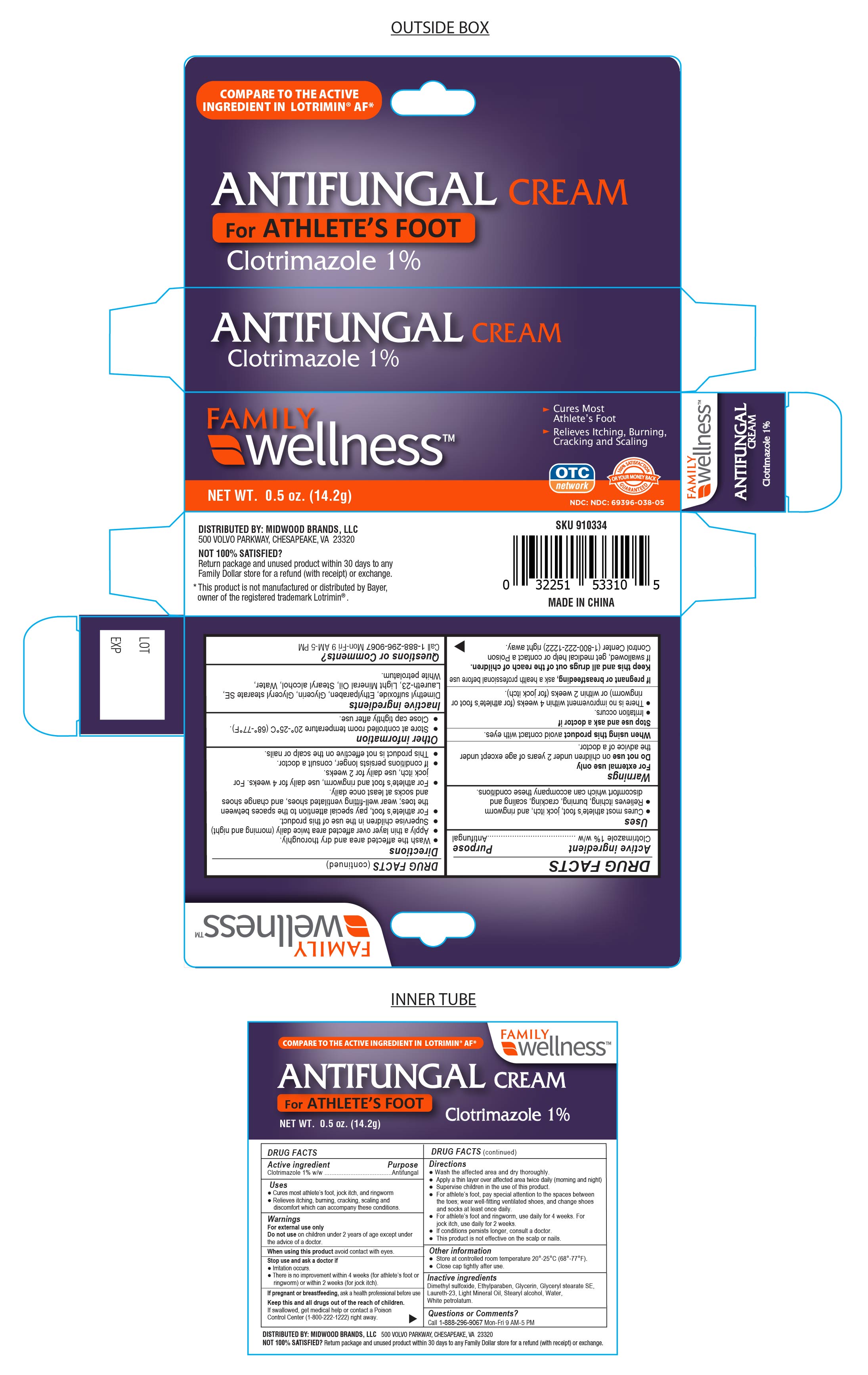 DRUG LABEL: Clotrimazole
NDC: 69396-038 | Form: CREAM
Manufacturer: Trifecta Pharmaceuticals USA LLC
Category: otc | Type: HUMAN OTC DRUG LABEL
Date: 20241213

ACTIVE INGREDIENTS: CLOTRIMAZOLE 1 g/100 g
INACTIVE INGREDIENTS: DIMETHYL SULFOXIDE; ETHYLPARABEN; GLYCERIN; GLYCERYL STEARATE SE; LAURETH-23; LIGHT MINERAL OIL; PETROLATUM; STEARYL ALCOHOL; WATER

Clotrimazole cream USP, 1%

Active ingredient

Clotrimazole USP 1% w/w

Purpose

Antifungal Cream

KEEP OUT OF REACH OF CHILDREN

Keep this and all drugs out of the reach of children. If swallowed get medical help or contact a Poison Control Center (1-800-222-1222) right away.

Uses

Cures athlete’s foot (tinea pedis), jock itch (tinea cruris), ringworm (tinea corporis). Relieves the itching, burning, cracking, scaling and discomfort which can accompany these conditions.

Warnings

● Do not use on children under 2 years of age except under the advice of a doctor.

● For external use only

● When using this product avoid contact with eyes.

Stop Use and ask a Doctor if:

- irritation occurs
- there is no improvement within 4 weeks (for Athlete's foot or ringwork) or within 2 weeks (for jock itch).

If Pregnant or breastfeeding, ask a health professional before use.

Directions

- Wash the affected area and dry thoroughly.

● Apply a thin layer of this product over affected area twice daily (morning and night), or as directed by a doctor.

● Supervise children in the use of this product.

● For athlete’s foot, pay special attention to the spaces between the toes; wear well-fitting ventilated shoes, and change shoes and socks at least once daily.

● For athlete’s foot and ringworm, use daily for 4 weeks. For jock itch, use daily for 2 weeks.

● If conditions persists longer, consult a doctor.

● This product is not effective on the scalp or nails.

Inactive Ingredients

Dimethyl Sulfoxide, Ethylparaben, Glycerin, Glyceryl Stearate SE, Laureth-23, Light Mineral Oil, Petrolatum, Stearyl Alcohol, Water

Other Information

- store at controlled room temperature 20°-25°C (68°- 77°F)
- Close cap tightly after use.

Questions or Comments?

Call 1-888-296-9067 Mon-Fri 9AM - 5PM

DISTRIBUTED BY: MIDWOOD BRANDS, LLC.

500 Volvo Parkway, Chesapeake, VA. 23320

NOT SATISFIED?

Return Package and unused product within 30 days to any Family Dollar store for a refund (with receipt) or exchange.

This product is not manufactured or distributed by Bayer, owner of the registered trademark Lotrimin®